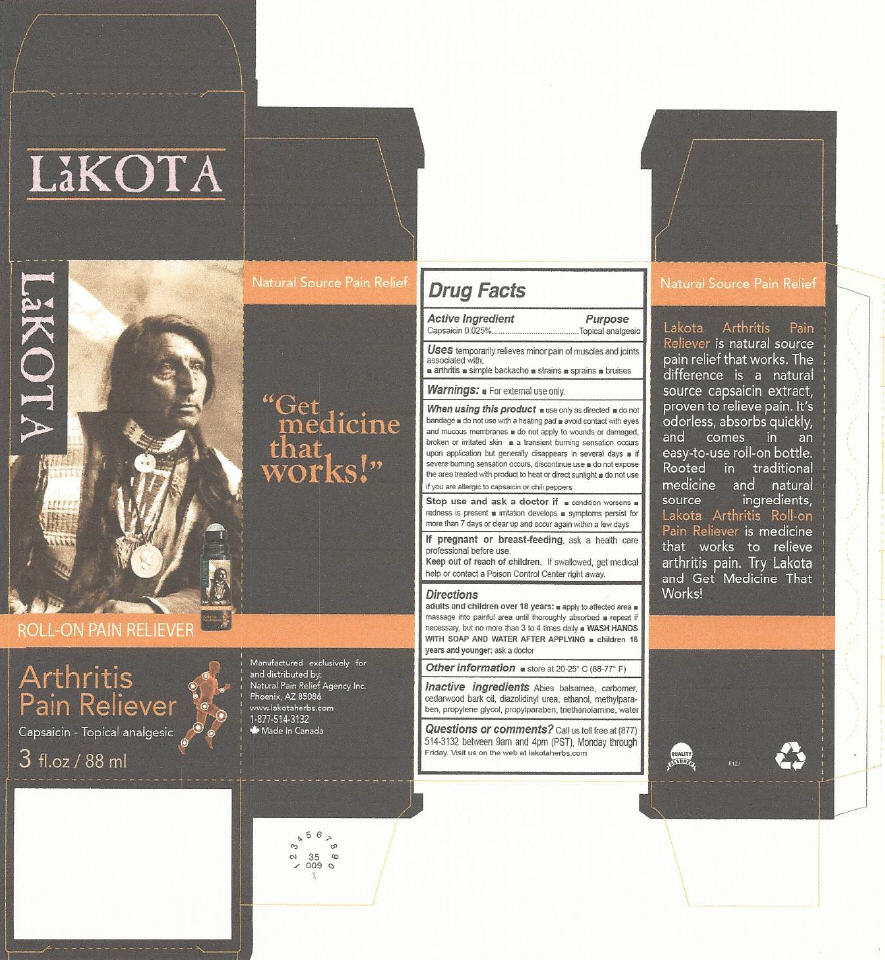 DRUG LABEL: Arthritis Pain Reliever
NDC: 59092-001 | Form: CREAM
Manufacturer: HPI Health Products Inc.
Category: otc | Type: HUMAN OTC DRUG LABEL
Date: 20131224

ACTIVE INGREDIENTS: capsaicin 0.25 mg/1 mL
INACTIVE INGREDIENTS: canada balsam; alcohol; carbomer interpolymer type A (allyl sucrose crosslinked); diazolidinyl urea; methylparaben; propylene glycol; propylparaben; trolamine; water; cedrus atlantica bark oil

Arthritis Pain Reliever

Drug Facts

Active Ingredient

Capsaicin 0.025%

Purpose

Topical analgesic

Uses

temporarily relieves minor pain of muscles and joints associated with:

- arthritis
- simple backache
- strains
- sprains
- bruises

Warnings

- For external use only.

When using this product

- use only as directed
- do not bandage
- do not use with a heating pad
- avoid contact with eyes and mucous membranes
- do not apply to wounds or damaged, broken or irritated skin
- a transient burning sensation occurs upon application but generally disappears in several days
- if severe burning sensation occurs, discontinue use
- do not expose the area treated with product to heat or direct sunlight
- do not use if you are allergic to capsaicin or chili peppers

Stop use and ask a doctor if

- condition worsens
- redness if present
- irritation develops
- symptoms persist for more than 7 days or clear up and occur again within a few days

PREGNANCY OR BREAST FEEDING

If pregnant or breast-feeding, ask a health care professional before use.

Keep out of reach of children. If swallowed, get medical help or contact a Poison Control Center right away.

Directions

adults and children over 18 years:

- apply to affected area
- massage into painful area until thoroughly absorbed
- repeat if necessary, but no more than 3 to 4 times daily
- WASH HANDS WITH SOAP AND WATER AFTER APPLYING
- Children 18 years and younger: ask a doctor

Other information

- store at 20-25°C (68-77°F)

Inactive ingredients

Abies balsamea, carbomer, cedarwood bark oil, diazolidinyl urea, ethanol, methylparaben, propylene glycol, propylparaben, triethanolamine, water

Questions or comments?

Call us toll-free at (877) 514-3132 between 9am and 4pm (PST), Monday through Friday. Visit us on the website at lakotaherbs.com

distributed by:
Natural Pain Relief Agency Inc.
Phoenix, AZ 85086

PRINCIPAL DISPLAY PANEL - 88 ml Bottle Carton

LaKOTA
Roll-On Pain Reliever

Arthritis Pain Releiver

Capsaicin – Topical analgesic

3 fl.oz/88ml